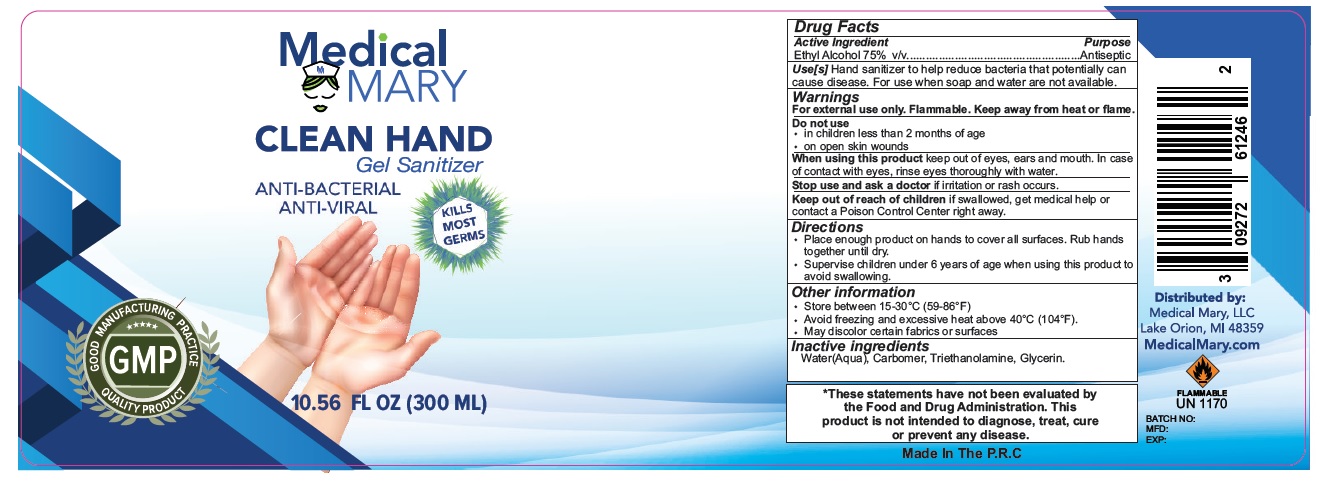 DRUG LABEL: MEDICAL MARY LLC
NDC: 73027-101 | Form: GEL
Manufacturer: JIANGSU HANHE DAILY CHEMICALS CO., LTD.
Category: otc | Type: HUMAN OTC DRUG LABEL
Date: 20200527

ACTIVE INGREDIENTS: ALCOHOL 75 mL/100 mL
INACTIVE INGREDIENTS: WATER; CARBOMER HOMOPOLYMER, UNSPECIFIED TYPE; TROLAMINE; GLYCERIN

Medical MARY CLEAN HAND Gel Sanitizer

Active Ingredient

Ethyl Alcohol 75% v/v

Purpose

Antiseptic

INDICATIONS AND USAGE

Use[s] Hand sanitizer to help reduce bacteria that potentially can cause disease. For use when soap and water are not available.

Warnings

For external use only. Flammable. Keep away from heat or flame.

Do not use

- in children less than 2 months of age
- on open skin wounds

When using this product keep out of eyes, ears and mouth. In case of contact with eyes, rinse eyes thoroughly with water.

Stop use and ask a doctor if irritation or rash occurs.

Keep out of reach of children if swallowed, get medical help or contact a Poison Control Center right away.

Directions

- Place enough product on hands to cover all surfaces. Rub hands together until dry.
- Supervise children under 6 years of age when using this product to avoid swallowing.

Other information

- Store between 15-30°C (59-86°F)
- Avoid freezing and excessive heat above 40°C (104°F).
- May discolor certain fabrics or surfaces

Inactive ingredients

Water(Aqua), Carbomer, Triethanolamine, Glycerin.

ANTI-BACTERIAL

ANTI-VIRAL

KILLS MOST GERMS

GOOD MANUFACTURING PRACTICE GMP QUALITY PRODUCT

Distributed by:

Medical Mary, LLC Lake Orion, MI 48359

MedicalMary.com

FLAMMABLE UN 1170

*These statements have not been evaluated by the Food and Drug Administration. This product is not intended to diagnose, treat, cure or prevent any disease.

Made in the P.R.C